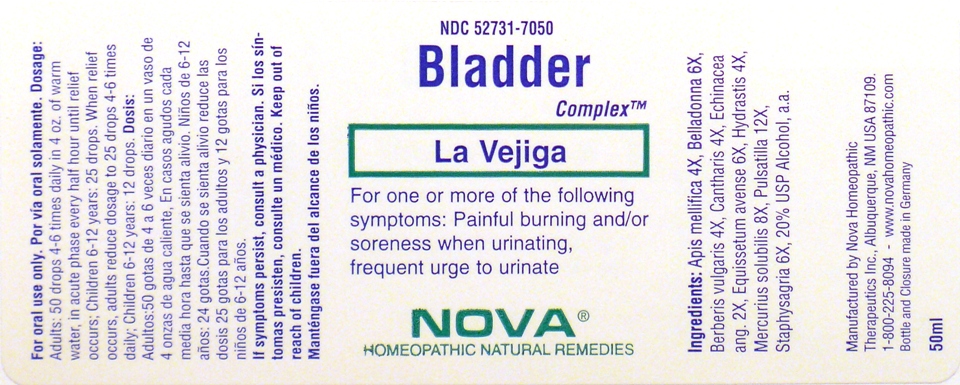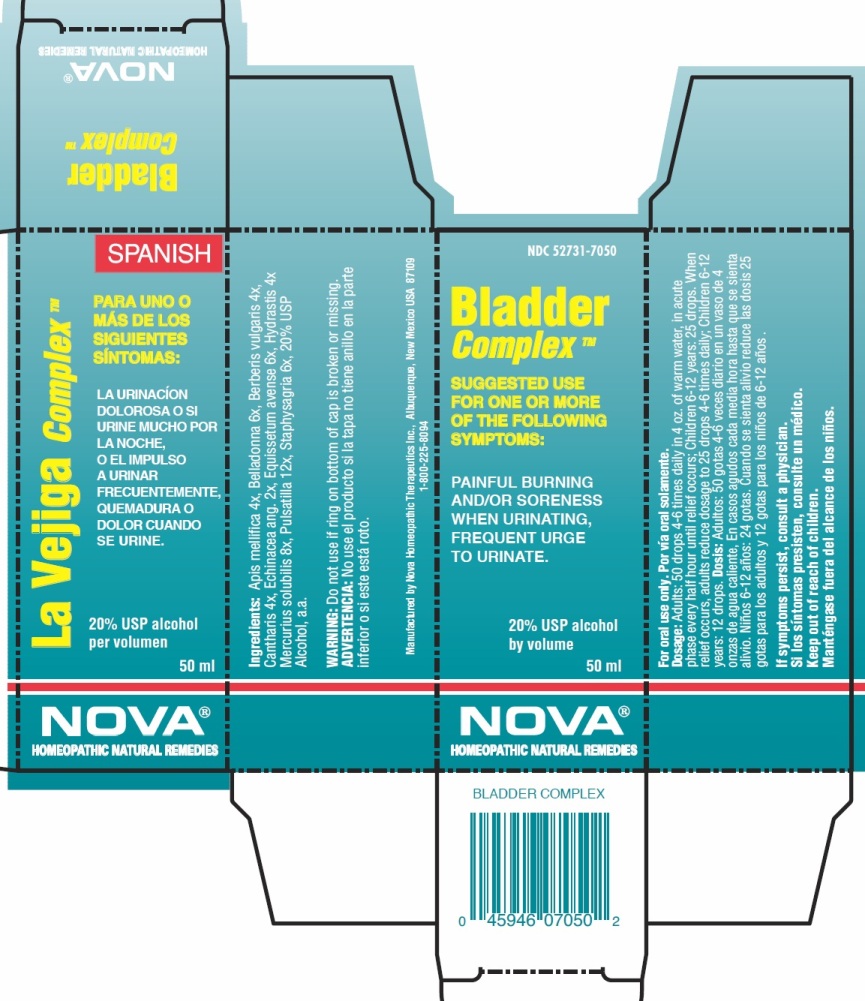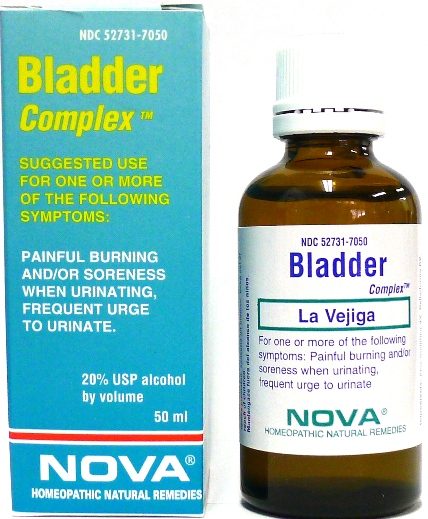 DRUG LABEL: Bladder Complex
NDC: 52731-7050 | Form: LIQUID
Manufacturer: Nova Homeopathic Therapeutics, Inc.
Category: homeopathic | Type: HUMAN OTC DRUG LABEL
Date: 20110601

ACTIVE INGREDIENTS: APIS MELLIFERA 4 [hp_X]/1 mL; ATROPA BELLADONNA 6 [hp_X]/1 mL; BERBERIS VULGARIS FRUIT 4 [hp_X]/1 mL; LYTTA VESICATORIA 4 [hp_X]/1 mL; ECHINACEA ANGUSTIFOLIA 2 [hp_X]/1 mL; EQUISETUM ARVENSE TOP 6 [hp_X]/1 mL; GOLDENSEAL 4 [hp_X]/1 mL; MERCURIUS SOLUBILIS 8 [hp_X]/1 mL; PULSATILLA VULGARIS 12 [hp_X]/1 mL; DELPHINIUM STAPHISAGRIA SEED 6 [hp_X]/1 mL
INACTIVE INGREDIENTS: ALCOHOL

Bladder Complex

Purpose:

Suggested use for one or more of the following symptoms:

Painful burning and/or soreness when urinating, frequent urge to urinate.

INDICATIONS AND USAGE

For oral use only.

DOSAGE AND ADMINISTRATION

Adults:
In Acute Phase:
50 drops in 4 oz. of warm water, every half hour until relief occurs
When Relief Occurs:
Reduce to 25 drops in 4 oz. of warm water, 4-6 times daily
Children 6-12 years:
In Acute Phase:
25 drops in 4 oz. of warm water, every half hour until relief occurs
When Relief Occurs:
Reduce to 12 drops in 4 oz. of warm water, 4-6 times daily

Warnings:

Keep out of reach of children.

WARNINGS

If symptoms persist, consult a physician.

Do not use if bottom of cap is broken or missing.

Active Ingredients:

Apis mellifica 4x, Belladonna 6x, Berberis vulgaris 4x,
Cantharis 4x, Echinacea ang. 2x, Equissetum avense 6x, Hydrastis 4x
Mercurius solubilis 8x, Pulsatilla 12x, Staphysagria 6x

Inactive Ingredients:

Alcohol, 20% USP

QUESTIONS

Manufactured by Nova Homeopathic Therapeutics Inc., Albuquerque, New Mexico USA 87109
1-800-225-8094

PACKAGE LABEL

Bladder Complex Product

Bladder Complex Bottle Label

Bladder Complex Box